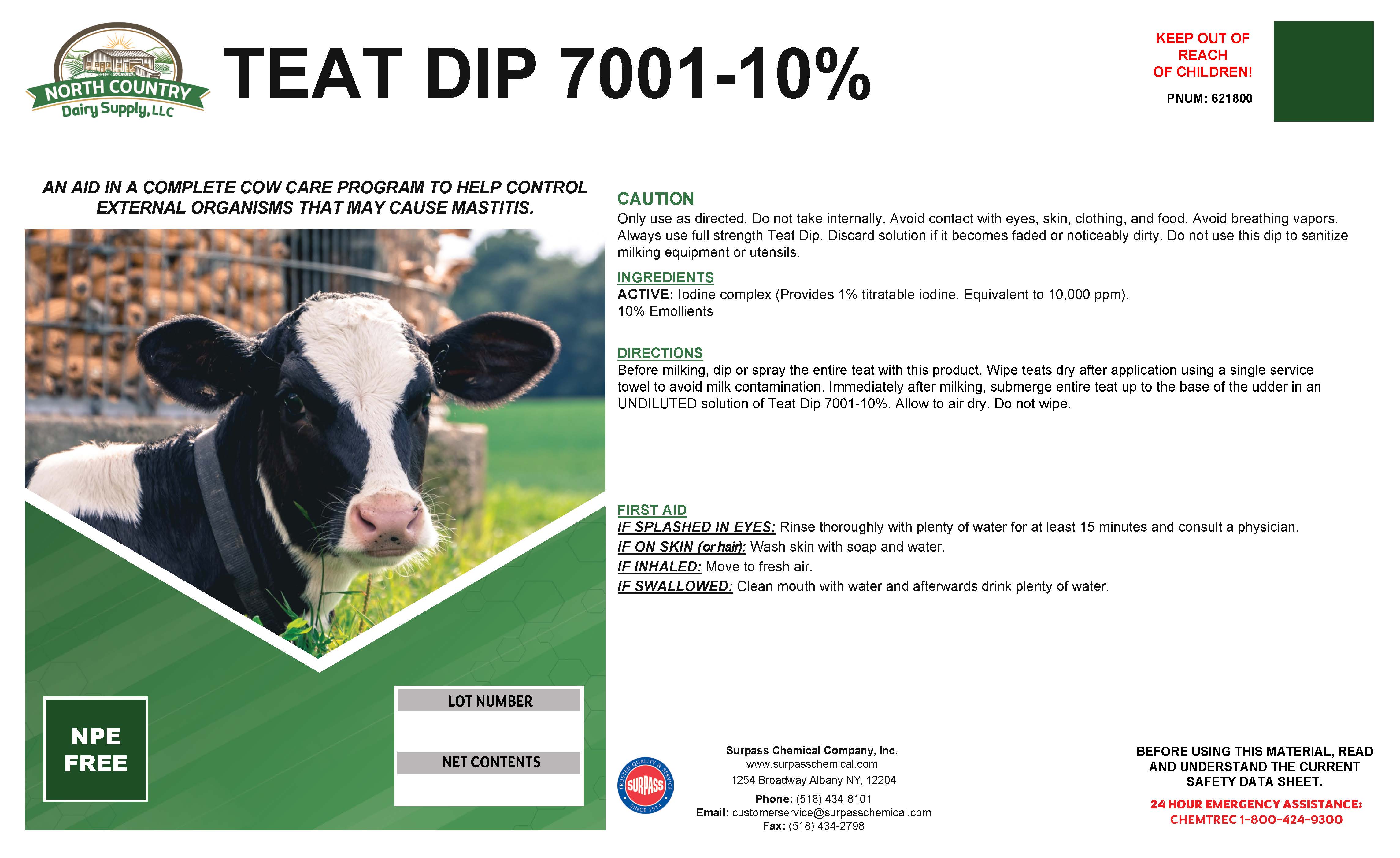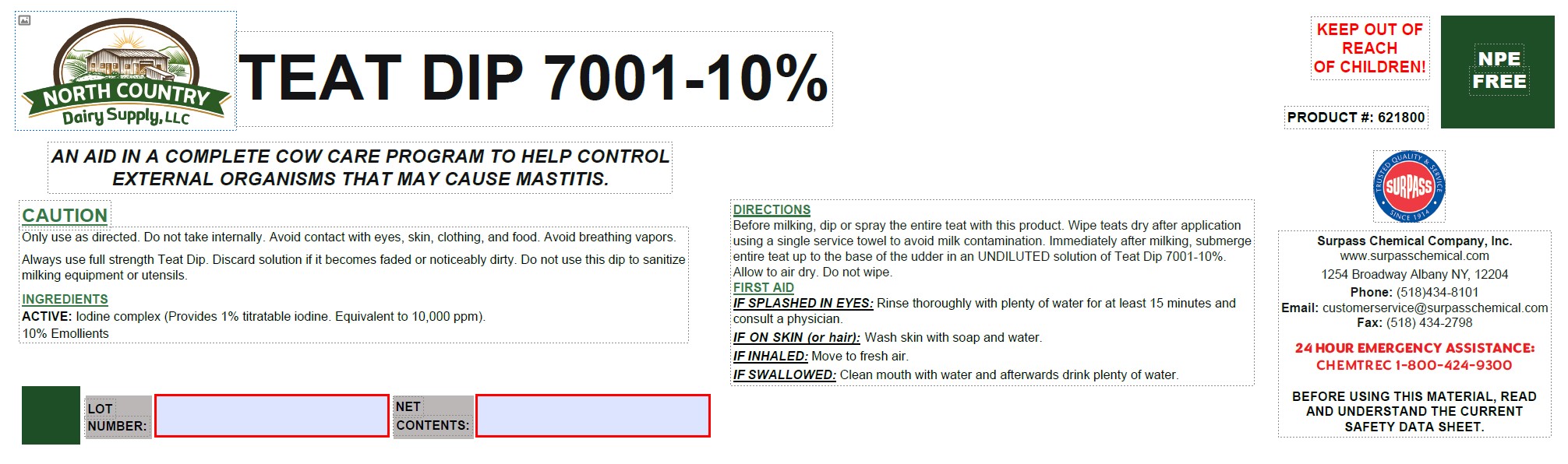 DRUG LABEL: Teat Dip 7001-10%
NDC: 86067-0116 | Form: SOLUTION
Manufacturer: Surpass Chemical Company, Inc.
Category: animal | Type: OTC ANIMAL DRUG LABEL
Date: 20251217

ACTIVE INGREDIENTS: IODINE 0.04724 kg/1 kg
INACTIVE INGREDIENTS: WATER 0.79396 kg/1 kg; C9-11 PARETH-8 0.051 kg/1 kg; GLYCERIN 0.0984 kg/1 kg; TRISODIUM CITRATE DIHYDRATE 0.007 kg/1 kg; XANTHAN GUM 0.0008 kg/1 kg; 1,3-BUTYLENE GLYCOL DIOLEATE 0.0016 kg/1 kg

Teat Dip 7001-10%

DESCRIPTION

TEAT DIP 7001-10%

An aid in a complete cow care program to help control external organisms that may cause mastitis. PRODUCT #: 621800

DIRECTIONS:
Only use as directed. Do not take internally. Avoid contact with eyes, skin, clothing, and food. Avoid breathing vapors. Always use full strength Teat Dip. Discard solution if it becomes faded or noticeably dirty. Do not use this dip to sanitize milking equipment or utensils.

GENERAL PRECAUTIONS

CAUTION:

Only use as directed. Do not take internally. Avoid contact with eyes, skin, clothing, and food. Avoid breathing vapors. Always use full strength Teat Dip. Discard solution if it becomes faded or noticeably dirty. Do not use this dip to sanitize milking equipment or utensils.

ACTIVE INGREDIENT

INGREDIENTS:
ACTIVE: Iodine complex (Provides 1% titratable iodine. Equivalent to 10,000 ppm).

OTHER SAFETY INFORMATION

FIRST AID:
IF SPLASHED IN EYES: Rinse immediately with plenty of water, also under the eyelids, for at least 15 minutes. Immediate medical attention is required.
IF ON SKIN (or hair): Wash off immediately with soap and plenty of water removing all contaminated clothes and shoes. Immediate medical attention is required.
IF INHALED: Move to fresh air. If breathing is difficult, give oxygen. Immediate medical attention is required.
IF SWALLOWED: Drink plenty of water. Never give anything by mouth to an unconscious person. Consult a physician if necessary.

SAFE HANDLING WARNING

BEFORE USING THIS MATERIAL, READ AND
UNDERSTAND THE CURRENT SAFETY DATA SHEET.

24 HOUR EMERGENCY ASSISTANCE:

CHEMTREC 1-800-424-9300

Surpass Chemical Company, Inc. Phone: (518) 434-8101 24 HOUR EMERGENCY ASSISTANCE:
www.surpasschemical.com Fax: (518) 434-2798 CHEMTREC 1-800-424-9300
1254 Broadway Albany NY, 12204 Email: customerservice@surpasschemical.com

KEEP OUT OF REACH
OF CHILDREN!